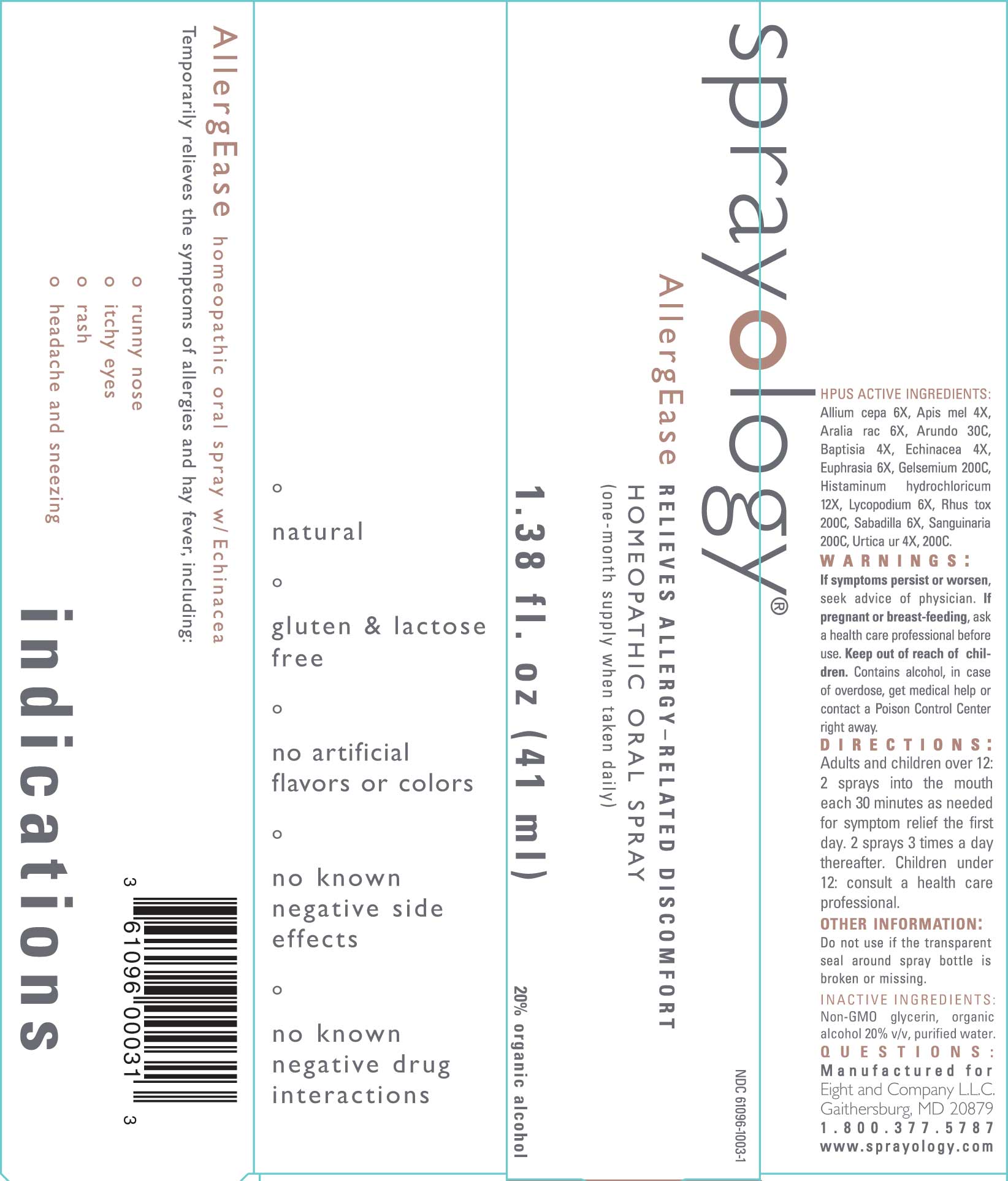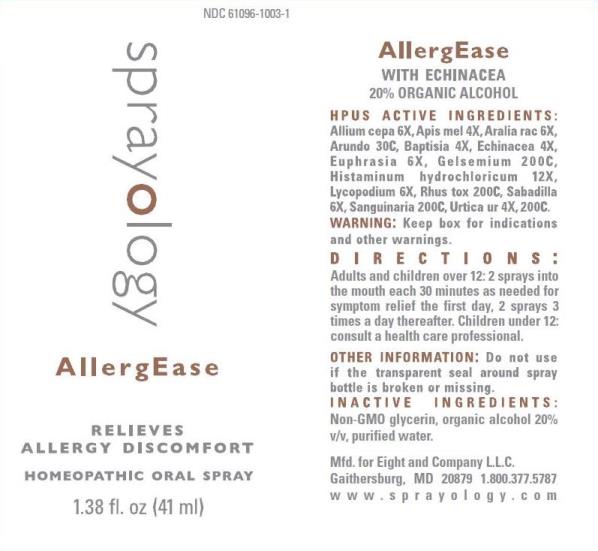 DRUG LABEL: AllergEase
NDC: 61096-1003 | Form: LIQUID
Manufacturer: Eight and Company L.L.C
Category: homeopathic | Type: HUMAN OTC DRUG LABEL
Date: 20251218

ACTIVE INGREDIENTS: ONION 6 [hp_X]/41 mL; APIS MELLIFERA 4 [hp_X]/41 mL; ARALIA RACEMOSA ROOT 6 [hp_X]/41 mL; ARUNDO PLINIANA ROOT 30 [hp_C]/41 mL; BAPTISIA TINCTORIA ROOT 4 [hp_X]/41 mL; ECHINACEA, UNSPECIFIED 4 [hp_X]/41 mL; EUPHRASIA STRICTA 6 [hp_X]/41 mL; GELSEMIUM SEMPERVIRENS ROOT 200 [hp_C]/41 mL; HISTAMINE DIHYDROCHLORIDE 12 [hp_X]/41 mL; LYCOPODIUM CLAVATUM SPORE 6 [hp_X]/41 mL; TOXICODENDRON PUBESCENS LEAF 200 [hp_C]/41 mL; SCHOENOCAULON OFFICINALE SEED 6 [hp_X]/41 mL; SANGUINARIA CANADENSIS ROOT 200 [hp_C]/41 mL; URTICA URENS WHOLE 200 [hp_C]/41 mL
INACTIVE INGREDIENTS: GLYCERIN; ALCOHOL; WATER

AllergEase

ACTIVE INGREDIENTS:

Allium cepa 6X, Apis mel 4X, Aralia rac 6X, Arundo 30C, Baptisia 4X, Echinacea 4X, Euphrasia 6X, Gelsemium 200C, Histaminum hydrochloricum 12X, Lycopodium 6X, Rhus Tox 200C, Sabadilla 6X, Sanguinaria 200C, Urtica Urens 4X, 200C.

PURPOSE:

Temporarily relieves the symptoms of allergies and hay fever, including:

° runny nose
° itchy eyes
° rash
° headache and sneezing

WARNINGS:

If symptoms persist or worsen, seek advice of physician. If pregnant or breast-feeding, ask a health care professional before use. Keep out of reach of children. Contains alcohol, in case of overdose, get medical help or contact a Poison Control Center right away.

Keep box for indications and other warnings.

Keep out of reach of children. Contains alcohol, in case of overdose, get medical help or contact a Poison Control Center right away.

DIRECTIONS:

Adults and children over 12: 2 sprays into the mouth each 30 minutes as needed for symptom relief the first day. 2 sprays 3 times a day thereafter. Children under 12 consult a health care professional.

OTHER INFORMATION:

Do not use if the transparent seal around spray bottle is broken or missing.

INDICATIONS:

Temporarily relieves the symptoms of allergies and hay fever, including:

° runny nose
° itchy eyes
° rash
° headache and sneezing
° natural

° gluten & lactose free

° no artifical flavors or colors

° no known negative side effects

° no known negative drug interactions

INACTIVE INGREDIENTS:

Non-GMO glycerin, organic alcohol 20% v/v, purified water.

QUESTIONS:

Mfd. for Eight and Company L.L.C.

Gaithersburg, MD 20879 1.800.377.5787

www.sprayology.com

PACKAGE LABEL DISPLAY:

sprayology

AllergEase

RELIEVES ALLERGY-RELATED DISCOMFORT

HOMEOPATHIC ORAL SPRAY

1.38 fl.oz (41 ml)